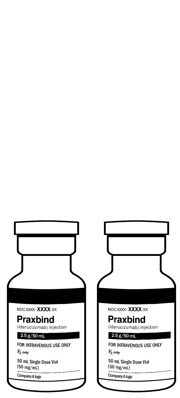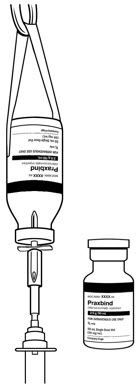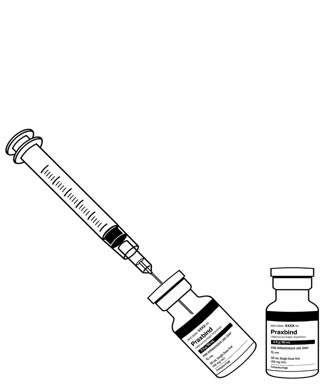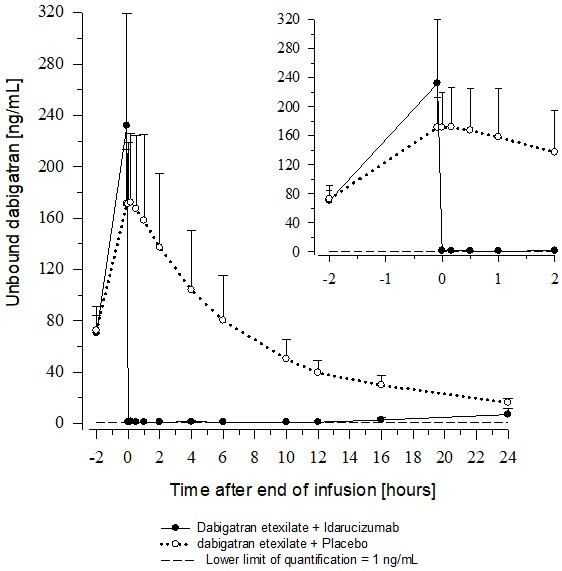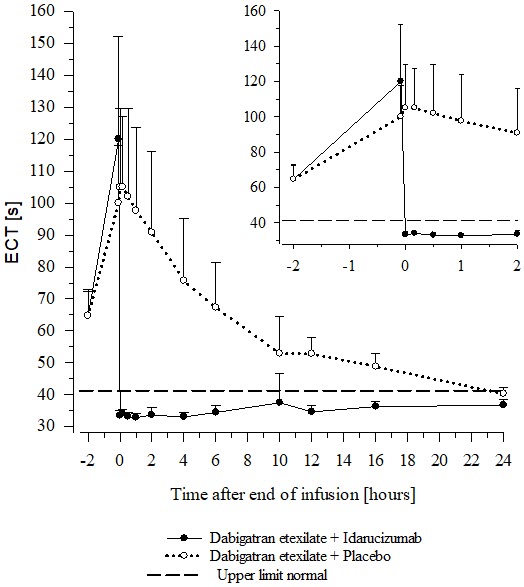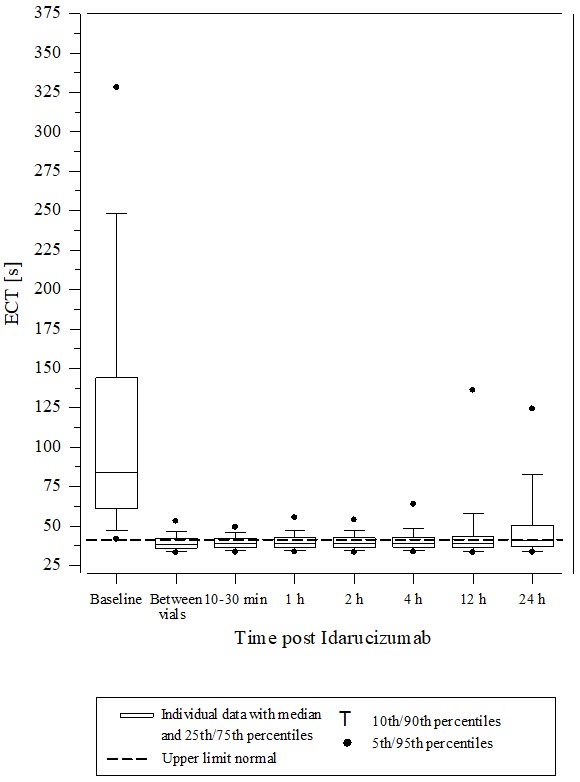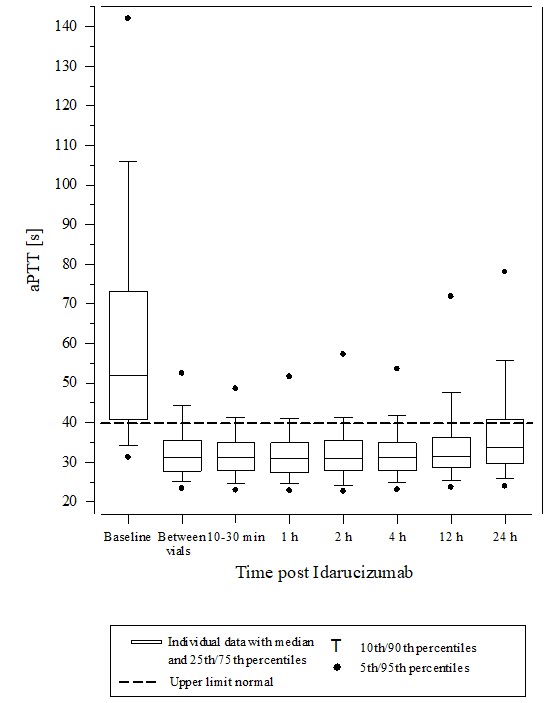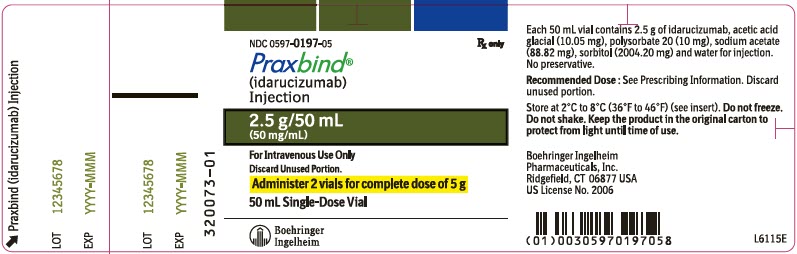 DRUG LABEL: Praxbind
NDC: 0597-0197 | Form: INJECTION
Manufacturer: Boehringer Ingelheim Pharmaceuticals, Inc.
Category: prescription | Type: HUMAN PRESCRIPTION DRUG LABEL
Date: 20240123

ACTIVE INGREDIENTS: IDARUCIZUMAB 50 mg/1 mL

HIGHLIGHTS OF PRESCRIBING INFORMATION

These highlights do not include all the information needed to use PRAXBIND safely and effectively. See full prescribing information for PRAXBIND.
PRAXBIND® (idarucizumab) injection, for intravenous use
Initial U.S. Approval: 2015

1 INDICATIONS AND USAGE

PRAXBIND is a humanized monoclonal antibody fragment (Fab) indicated in patients treated with Pradaxa® when reversal of the anticoagulant effects of dabigatran is needed:

- For emergency surgery/urgent procedures
- In life-threatening or uncontrolled bleeding (1)

2 DOSAGE AND ADMINISTRATION

For intravenous use only.

- The recommended dose of PRAXBIND is 5 g, provided as two separate vials each containing 2.5 g/50 mL idarucizumab. (2.1)
- There is limited data to support administration of an additional 5 g of PRAXBIND. (2.1)

3 DOSAGE FORMS AND STRENGTHS

Injection: 2.5 g/50 mL solution in a single-dose vial (3)

4 CONTRAINDICATIONS

None (4)

5 WARNINGS AND PRECAUTIONS

- Thromboembolic Risk: Reversing dabigatran therapy exposes patients to the thrombotic risk of their underlying disease. Resume anticoagulant therapy as soon as medically appropriate. (2.4, 5.1)
- Re-elevation of Coagulation Parameters: In patients with elevated coagulation parameters and reappearance of clinically relevant bleeding or requiring a second emergency surgery/urgent procedure, an additional 5 g dose of PRAXBIND may be considered. (5.2)
- Hypersensitivity reactions: Discontinue administration and evaluate. (5.3)
- Risks of Serious Adverse Reactions in Patients with Hereditary Fructose Intolerance due to Sorbitol Excipient: Patients with hereditary fructose intolerance may be at risk of adverse reactions. (5.4)

6 ADVERSE REACTIONS

- In healthy volunteers, the most frequently reported adverse reactions in ≥5% of subjects treated with idarucizumab was headache. (6.1)
- In patients, the most frequently reported adverse reactions in ≥5% of patients treated with idarucizumab were constipation and nausea. (6.1)

To report SUSPECTED ADVERSE REACTIONS, contact Boehringer Ingelheim Pharmaceuticals, Inc. at 1-800-542-6257 or FDA at 1-800-FDA-1088 or www.fda.gov/medwatch.

FULL PRESCRIBING INFORMATION

1 INDICATIONS AND USAGE

PRAXBIND is indicated in patients treated with Pradaxa when reversal of the anticoagulant effects of dabigatran is needed:

- For emergency surgery/urgent procedures
- In life-threatening or uncontrolled bleeding

2 DOSAGE AND ADMINISTRATION

2.1 Recommended Dose

The recommended dose of PRAXBIND is 5 g, provided as two separate vials each containing 2.5 g/50 mL idarucizumab (see Figure 1). Both vials are packaged together in one carton.

For intravenous use only.

There is limited data to support administration of an additional 5 g of PRAXBIND [see Warnings and Precautions (5.2)].

2.2 Preparation

- Remove both vials (each containing 2.5 g/50 mL idarucizumab) from carton.
- Ensure aseptic handling when preparing the infusion.
- Parenteral drug products should be inspected visually for particulate matter and discoloration prior to administration, whenever solution and container permit.
- Once solution has been removed from the vial, administration should begin promptly. The solution in vials may be stored at room temperature, 25°C (77°F), but must be used within 6 hours [see How Supplied/Storage and Handling (16.2)].

2.3 Administration

- Do not mix with other medicinal products. Use aseptic technique when administering PRAXBIND.
- Intravenously administer the dose of 5 g (2 vials, each contains 2.5 g) as
  - Two consecutive infusions (see Figure 2) or
  - Bolus injection by injecting both vials consecutively one after another via syringe (see Figure 3).
- A pre-existing intravenous line may be used for administration of PRAXBIND. The line must be flushed with sterile 0.9% Sodium Chloride Injection, USP solution prior to infusion. No other infusion should be administered in parallel via the same intravenous access.
- PRAXBIND treatment can be used in conjunction with standard supportive measures, which should be considered as medically appropriate [see Clinical Pharmacology (12.2)].

Figure 1 Recommended dose of PRAXBIND provided as two vials.

Figure 2 Two consecutive infusions by hanging vials.

Figure 3 Inject both vials consecutively via syringe.

2.4 Restarting Antithrombotic Therapy

Patients being treated with dabigatran therapy have underlying disease states that predispose them to thromboembolic events. Reversing dabigatran therapy exposes patients to the thrombotic risk of their underlying disease. To reduce this risk, resumption of anticoagulant therapy should be considered as soon as medically appropriate.

Idarucizumab is a specific reversal agent for dabigatran, with no impact on the effect of other anticoagulant or antithrombotic therapies.

Pradaxa treatment can be initiated 24 hours after administration of PRAXBIND [see Clinical Pharmacology (12.2)].

3 DOSAGE FORMS AND STRENGTHS

PRAXBIND is a sterile, preservative-free, colorless to slightly yellow, clear to slightly opalescent solution available as:

Injection: 2.5 g/50 mL solution in a single-dose vial.

4 CONTRAINDICATIONS

None.

5 WARNINGS AND PRECAUTIONS

5.1 Thromboembolic Risk

Patients being treated with dabigatran therapy have underlying disease states that predispose them to thromboembolic events. Reversing dabigatran therapy exposes patients to the thrombotic risk of their underlying disease. To reduce this risk, resumption of anticoagulant therapy should be considered as soon as medically appropriate [see Dosage and Administration (2.4)].

5.2 Re-elevation of Coagulation Parameters

In a limited number of patients in the clinical program, between 12 and 24 hours after administration of 5 g idarucizumab, elevated coagulation parameters (e.g., activated partial thromboplastin time (aPTT) or ecarin clotting time (ECT)) have been observed [see Dosage and Administration (2.1)].

If reappearance of clinically relevant bleeding together with elevated coagulation parameters is observed after administration of 5 g PRAXBIND, administration of an additional 5 g dose of PRAXBIND may be considered. Similarly, patients who require a second emergency surgery/urgent procedure and have elevated coagulation parameters may receive an additional 5 g dose of PRAXBIND.

The safety and effectiveness of repeat treatment with PRAXBIND have not been established [see Clinical Pharmacology (12.2)].

5.3 Hypersensitivity Reactions

There is insufficient clinical experience with PRAXBIND in patients to evaluate risk of hypersensitivity to idarucizumab. In clinical studies adverse events possibly indicative of hypersensitivity reactions where a possible relationship could not be excluded were reported [see Adverse Reactions (6.1)]. The risk of using PRAXBIND in patients with known hypersensitivity (e.g., anaphylactoid reaction) to idarucizumab or to any of the excipients needs to be weighed cautiously against the potential benefit of such an emergency treatment. If an anaphylactic reaction or other serious allergic reaction occurs, immediately discontinue administration of PRAXBIND and institute appropriate treatment.

5.4 Risks of Serious Adverse Reactions in Patients with Hereditary Fructose Intolerance due to Sorbitol Excipient

In patients with the condition of hereditary fructose intolerance who have received parenteral administration of sorbitol, serious adverse reactions, including fatal reactions, have been reported. Reactions have included hypoglycemia, hypophosphatemia, metabolic acidosis, increase in uric acid, acute liver failure with breakdown of excretory and synthetic function.

The recommended dose of PRAXBIND contains 4 g sorbitol as an excipient. When prescribing PRAXBIND to patients with hereditary fructose intolerance, consider the combined daily metabolic load of sorbitol/fructose from all sources, including PRAXBIND and other drugs containing sorbitol. The minimum amount of sorbitol at which serious adverse reactions may occur in these patients is not known.

6 ADVERSE REACTIONS

The following serious adverse reactions are described in more detail elsewhere in the labeling:

- Thromboembolic Risk [see Warnings and Precautions (5.1)]
- Hypersensitivity Reactions [see Warnings and Precautions (5.3)]
- Risks of Serious Adverse Reactions in Patients with Hereditary Fructose Intolerance due to Sorbitol Excipient [see Warnings and Precautions (5.4)]

6.1 Clinical Trials Experience

Because clinical trials are conducted under widely varying conditions, adverse reaction rates observed in the clinical trials of a drug cannot be directly compared to rates in the clinical trials of another drug and may not reflect the rates observed in clinical practice.

In three healthy volunteer clinical trials, 224 subjects were treated with idarucizumab. In these trials, during the treatment period, the overall frequency of adverse events was similar between idarucizumab-treated subjects (55/224, 25%) and placebo-treated subjects (26/105, 25%). Among those subjects treated with idarucizumab, adverse reactions reported in ≥5% of subjects was headache (12/224, 5%).

In the RE-VERSE-AD® (RE-VERSal Effects of idarucizumab on Active Dabigatran) trial, a total of 503 dabigatran-treated patients were administered idarucizumab either because they required an emergency surgery or urgent procedure, or because they presented with life-threatening or uncontrolled bleeding [see Clinical Studies (14)]. The adverse reactions reported in ≥5% of patients were constipation (33/503, 7%) and nausea (23/503, 5%). Of the 503 dabigatran-treated patients in the entire study period, 101 patients died, 19 within the first day after idarucizumab dosing; each of these deaths could be attributed either as a complication of the index event or associated with co-morbidities.

Thromboembolic Events

In the RE-VERSE-AD trial, 33 of 503 patients reported thrombotic events, 11 patients within 5 days after treatment with idarucizumab and 22 patients 6 days or more after treatment with idarucizumab. Most of these patients were not on antithrombotic therapy at the time of the event, and in each of these cases, the thrombotic event could be attributed to the underlying medical condition of the patient [see Warnings and Precautions (5.1)].

Hypersensitivity

Pyrexia, bronchospasm, hyperventilation, rash, and pruritus have been reported in clinical trials with idarucizumab [see Warnings and Precautions (5.3)].

6.2 Immunogenicity

As with all proteins there is a potential for immunogenicity with idarucizumab. Detection of antibody formation is highly dependent on the sensitivity and specificity of the assay. Additionally, the observed incidence of antibody (including neutralizing antibody) positivity in an assay may be influenced by several factors including assay methodology, sample handling, timing of sample collection, concomitant medications and underlying disease. For these reasons, comparison of the incidence of antibodies to idarucizumab in the studies described below with the incidence of antibodies in other studies or to other products may be misleading.

Using an electro-chemiluminescence (ECL) based assay, plasma samples from 283 subjects (224 treated with idarucizumab) in phase I trials and 501 patients were tested for antibodies cross-reacting with idarucizumab. Pre-existing antibodies with cross-reactivity to idarucizumab were detected in approximately 12% (33/283) of the subjects and 4% (19/501) of patients. The majority of pre-existing antibodies were shown to have low titers. No impact on the pharmacokinetics or the reversal effect of idarucizumab or hypersensitivity reactions were observed. Treatment-emergent possibly persisting anti-idarucizumab antibodies with low titers were observed in 4% (10/224) of the subjects and 2% (8/501) of patients treated with idarucizumab. Nine patients were re-dosed with idarucizumab. All nine patients were re-dosed within 6 days after the first idarucizumab dose. None of these patients re-dosed with idarucizumab tested positive for anti-idarucizumab antibodies.

The epitope specificity of antibodies to idarucizumab was characterized using probe molecules. For pre-existing antibodies in patients, 95% (18/19) had specificity for the C-terminus, a region of idarucizumab to which dabigatran does not bind. For treatment emergent antibodies in patients, 67% (6/9) had specificity for the C-terminus, 22% (2/9) had specificity for the variable region, and 11% (1/9) had mixed specificity.

8 USE IN SPECIFIC POPULATIONS

8.1 Pregnancy

Risk Summary

There are no available data on PRAXBIND use in pregnant women to inform a drug-associated risk of major birth defects and miscarriage. Animal reproductive and development studies have not been conducted with idarucizumab. It is also not known whether PRAXBIND can cause fetal harm when administered to a pregnant woman or can affect reproduction capacity. PRAXBIND should be given to a pregnant woman only if clearly needed.

The background risk of major birth defects and miscarriage for the indicated population is unknown. Adverse outcomes in pregnancy occur regardless of the health of the mother or the use of medications. In the U.S. general population, the estimated background risk of major birth defects and miscarriage in clinically recognized pregnancies is 2-4% and 15-20%, respectively.

8.2 Lactation

Risk Summary

There are no data on the effects of PRAXBIND on the breastfed child or on milk production.

It is not known whether idarucizumab is excreted in human milk. Because many drugs are excreted in human milk, caution should be exercised when PRAXBIND is administered to a nursing woman.

The developmental and health benefits of breastfeeding should be considered along with the mother's clinical need for PRAXBIND and any potential adverse effects on the breastfed child from PRAXBIND or from the underlying maternal condition.

8.4 Pediatric Use

Safety and effectiveness have not been established in pediatric patients.

8.5 Geriatric Use

A total of 454 (90%) patients treated with idarucizumab in the case series trial were 65 years of age and older, and 318 (63%) were 75 years of age and older. No overall differences in safety or effectiveness were observed between these subjects and younger subjects, and other reported clinical experience has not identified differences in responses between the elderly and younger patients, but greater sensitivity of some older individuals cannot be ruled out.

11 DESCRIPTION

Idarucizumab is a humanized monoclonal antibody fragment (Fab) derived from an IgG1 isotype molecule, whose target is the direct thrombin inhibitor dabigatran. Using recombinant expression technology, idarucizumab is produced in a well characterized recombinant (mammalian) CHO cell line and is purified using standard technology. Idarucizumab is composed of a light chain of 219 amino acids and a heavy chain fragment of 225 amino acids, covalently linked together by one disulfide bond between cysteine 225 of the heavy chain fragment and cysteine 219 of the light chain, and has an estimated molecular mass of approximately 47,766 Daltons.

PRAXBIND (idarucizumab) is a sterile, preservative-free, colorless to slightly yellow, clear to slightly opalescent solution for intravenous administration. PRAXBIND (idarucizumab) is supplied in 2 single-dose vials, each containing 2.5 g of idarucizumab in 50 mL formulated as a buffered, isotonic, solution containing acetic acid glacial (10.05 mg), polysorbate 20 (10 mg), sodium acetate (88.82 mg), sorbitol (2004.20 mg), and water for injection with an osmolality of 270-330 mOsm/kg and a pH of 5.3-5.7.

12 CLINICAL PHARMACOLOGY

12.1 Mechanism of Action

Idarucizumab is a specific reversal agent for dabigatran. It is a humanized monoclonal antibody fragment (Fab) that binds to dabigatran and its acylglucuronide metabolites with higher affinity than the binding affinity of dabigatran to thrombin, neutralizing their anticoagulant effect.

12.2 Pharmacodynamics

In healthy subjects aged 45 to 64 years, the plasma concentrations of unbound dabigatran were reduced to below the lower limit of quantification immediately after the administration of 5 g idarucizumab. Subjects' diluted thrombin time (dTT), ECT, aPTT, thrombin time (TT), and activated clotting time (ACT) parameters returned to baseline levels (see Figure 4 and Figure 5). This reduction of dabigatran plasma concentration was observed over the entire observation period of at least 24 hours. Similar findings were also observed in elderly subjects (aged 65 to 80 years) as well as subjects with mild and moderate renal impairment [see Clinical Pharmacology (12.3)].

In a limited number of patients, re-distribution of dabigatran from the periphery to plasma led to re-elevation of dTT, ECT, aPTT, and TT [see Warnings and Precautions (5.2)].

Re-dosing with 2.5 g idarucizumab in 6 healthy subjects aged 45-64 years at 2 months after first infusion revealed no differences in safety and no indication of allergic reactions [see Clinical Pharmacology (12.3)].

No changes in the pharmacokinetics or pharmacodynamics of dabigatran were noted upon re-initiation 24 hours after the administration of idarucizumab [see Dosage and Administration (2.4)].

Figure 4 Plasma-Levels of Unbound Dabigatran in the Representative Group of Healthy Subjects (Administration of Idarucizumab or Placebo at 0 h)

Figure 5 Change of ECT from Baseline in the Representative Group of Healthy Subjects (Administration of Idarucizumab or Placebo at 0 h)

Thrombin Generation Parameters

Idarucizumab alone has shown no procoagulant effect measured as endogenous thrombin potential (ETP).

Cardiac Electrophysiology

Clinical trials with idarucizumab in healthy subjects measured heart rate and electrocardiogram (ECG) parameters (waveform morphology, P wave duration, and PR, QRS, QT, and QTc intervals). There were no clinically relevant abnormal findings related to ECG.

Drug Interactions

In vitro Assessment of Drug Interactions

In vitro data suggest that the inhibition of dabigatran by idarucizumab is not affected by coagulation factor concentrates [3- or 4-factor prothrombin complex concentrates (PCCs), activated PCC, or recombinant Factor VIIa].

Assessment of Drug Interactions in Animal Studies

The potential effect of the binding of idarucizumab to dabigatran in the presence of volume replacement agents (e.g., crystalloids, colloids, and retransfusion of washed red blood cells) was investigated in swine. The results of this study suggest that neutralization of dabigatran anticoagulant activity is not influenced by 50% hemodilution with routinely used volume replacement strategies.

12.3 Pharmacokinetics

There were no obvious differences in the idarucizumab plasma concentration time profiles when idarucizumab was administered alone or after pretreatment with dabigatran. A dose-dependent increase in the fraction of unchanged idarucizumab excreted in urine was observed.

Distribution

Idarucizumab exhibited multiphasic disposition kinetics and limited extravascular distribution. Following the intravenous infusion of a 5 g dose, the geometric mean volume of distribution at steady state (Vss) was 8.9 L (geometric coefficient of variation (gCV 24.8%)).

Elimination

Idarucizumab was rapidly eliminated with a total clearance of 47.0 mL/min (gCV 18.4%), an initial half-life of 47 minutes (gCV 11.4%), and a terminal half-life of 10.3 h (gCV 18.9%). After intravenous administration of 5 g idarucizumab, 32.1% (gCV 60.0%) of the dose was recovered in urine within a collection period of 6 hours and less than 1% in the following 18 hours. The remaining part of the dose is assumed to be eliminated via protein catabolism, mainly in the kidney.

Metabolism

Several pathways have been described that may contribute to the metabolism of antibodies. All of these pathways involve biodegradation of the antibody to smaller molecules, i.e., small peptides or amino acids which are then reabsorbed and incorporated in the general protein synthesis.

Specific Populations

Age, Sex, Race and Body Weight

Age, sex, race (Caucasian vs Asian) and body weight had no clinically important effect on systemic exposure of idarucizumab based on population pharmacokinetic analyses which included data from 220 volunteers and 486 patients.

Patients with Renal Impairment

Idarucizumab has been studied in 12 subjects with mild renal impairment (creatinine clearance [CrCl] 60 to <90 mL/min, by Cockcroft-Gault equation) and 6 subjects with moderate impairment (CrCl30 to <60 mL/min). Compared to healthy subjects, the total clearance was reduced, leading to an increase in idarucizumab's area under the curve (AUC) by 43.5% and 83.5% in mild and moderate renal impairment, respectively. No dose adjustment is required in renally impaired patients.

Based on pharmacokinetic data from 347 patients with varying degrees of renal function (median CrCl 21 to 99 mL/min) it is estimated that mean idarucizumab exposure (AUC0–24h) increased by 38%, 90%, and 146% in patients with mild renal impairment (CrCl 50 to <80 mL/min), moderate renal impairment (CrCl 30 to <50 mL/min) and severe renal impairment (CrCl 0 to <30 mL/min), respectively. Since dabigatran is also excreted primarily via the kidneys, increases in the exposure to dabigatran are also seen with worsening renal function.

13 NONCLINICAL TOXICOLOGY

13.1 Carcinogenesis, Mutagenesis, Impairment of Fertility

No carcinogenicity or genotoxicity studies have been conducted with idarucizumab. No animal studies have been performed to evaluate the potential effects of idarucizumab on fertility in males or females or on reproduction and development.

14 CLINICAL STUDIES

The safety and effectiveness of PRAXBIND was investigated in three randomized placebo-controlled healthy volunteer trials, Trials 1321.1, 1321.2 and 1321.5 (NCT01688830, NCT01955720, NCT02028780), and in RE-VERSE-AD (RE-VERSal Effects of idarucizumab on Active Dabigatran) trial (NCT02104947), a single cohort case series trial with dabigatran-treated patients who have life-threatening or uncontrolled bleeding, or who require emergency surgery or urgent procedure.

Healthy Volunteers

Trials 1321.1, 1321.2 and 1321.5 in a total of 283 subjects assessed the safety, dose-response, and effect of idarucizumab on reducing unbound dabigatran and coagulation parameters. Of the 283 subjects, 224 received at least one dose of idarucizumab. These trials included 19 females and 30 subjects aged 65 years or older (overall mean age 36 years).

The tables below summarize the idarucizumab effect on coagulation parameters dTT, aPTT, ECT, TT, and ACT over time for 14 subjects treated in Trial 1321.2. Fourteen subjects received dabigatran 220 mg orally twice daily for three days and an additional single 220 mg dose of dabigatran on day four, two hours before receiving idarucizumab. Idarucizumab was administered as one 5 g intravenous infusion over five minutes. Table 1 shows the results of the idarucizumab treatment group and Table 2 shows the results of the placebo treatment group.

Table 1 Change in Coagulation Parameters in 14 Dabigatran-exposed Subjects Treated with 5 g Idarucizumab
Clotting Assay (Mean and Standard Deviation) | Pre-Idarucizumab (N=14) | End of infusion of Idarucizumab (N=14) | 24 hours after Idarucizumab (N=14)
dTT [s] | 66.6 (12.0) | 32.1 (1.38) | 33.0 (1.69)
aPTT [s] | 67.8 (14.5) | 29.2 (4.74) | 31.9 (5.71)
ECT [s] | 122 (42.2) | 34.7 (1.92) | 38.8 (2.86)
TT [s] | 127 (62.6) | 12.5 (0.786) | 19.3 (5.14)
ACT [s] | 236 (47.6) | 116 (7.71) | 140 (10.1)

Table 2 Change in Coagulation Parameters in 14 Dabigatran-exposed Subjects Treated with Placebo
Clotting Assay (Mean and Standard Deviation) | Pre-Placebo (N=14) | End of infusion of Placebo (N=14) | 24 hours after Placebo (N=14)
dTT [s] | 64.7 (9.82) | 65.3 (12.1) | 36.1 (2.48)
aPTT [s] | 65.2 (14.0) | 66.5 (13.2) | 37.0 (7.10)
ECT [s] | 117 (29.8) | 122 (32.9) | 44.7 (5.39)
TT [s] | 132 (35.4) | 147 (46.7) | 39.5 (11.8)
ACT [s] | 219 (44.7) | 216 (50.5) | 148 (15.1)

The effect of idarucizumab on reducing unbound dabigatran in healthy volunteers is summarized in section 12.2, Pharmacodynamics.

RE-VERSE-AD Patient Experience

In RE-VERSE-AD, 5 g idarucizumab was administered to patients treated with dabigatran who presented with dabigatran-related life-threatening or uncontrolled bleeding (Group A) or who required emergency surgery or urgent procedures (Group B). The primary endpoint was the maximum percentage reversal of the pharmacodynamic anticoagulant effect of dabigatran within 4 hours after the administration of idarucizumab, based on central laboratory determination of dTT or ECT.

RE-VERSE-AD included data for 503 patients: 301 patients with serious bleeding (Group A) and 202 requiring an urgent procedure (Group B). Approximately half of the patients in each group were male. The median age was 78 years and the median creatinine clearance was 53 mL/min. Approximately 62% of patients in Group A and 62% of patients in Group B had been treated with dabigatran 110 mg BID.

Reversal was evaluable only for those patients showing prolonged coagulation times prior to idarucizumab treatment. Among the evaluable patients, the median maximum reversal of the pharmacodynamic anticoagulant effect of dabigatran as measured by ECT, aPTT or dTT in the first 4 hours after administration of 5 g idarucizumab was 100%, with most patients achieving complete reversal as measured by ECT (82%), aPTT (93%) or dTT (99%). Reversal of the pharmacodynamics effects was evident immediately after administration. Results for Groups A and B were similar. In a limited number of patients, between 12 and 24 hours after administration of 5 g idarucizumab, elevated coagulation parameters (e.g., aPTT or ECT) have been observed. Eight patients were treated with more than 5 g idarucizumab due to rebleeding, a second emergency procedure and/or bleeding after an emergency surgical procedure. ECT measures over the 24-hour observation time are shown in Figure 6.

Figure 6 Change of ECT from Baseline in Dabigatran-exposed Patients (n=487)

Activated partial thromboplastin time (aPTT) showed similar results to ECT (see Figure 7).

Figure 7 Change of aPTT from Baseline in Dabigatran-exposed Patients (n=486)

16 HOW SUPPLIED/STORAGE AND HANDLING

16.1 How Supplied

- PRAXBIND is a sterile, preservative-free, colorless to slightly yellow, clear to slightly opalescent solution supplied as 2 single-dose vials each containing 2.5 g/50 mL of idarucizumab.
- NDC number 0597-0197-05: Carton containing two 2.5 g/50 mL vials.

16.2 Storage and Handling

- Store PRAXBIND vials in the refrigerator at 2°C to 8°C (36°F to 46°F) in the original carton to protect from light. Do not freeze. Do not shake.
- PRAXBIND vials may be stored at room temperature, 25°C (77°F), for up to 48 hours in the original carton to protect from light.
- PRAXBIND vials may be stored at room temperature, 25°C (77°F), out of the carton and exposed to light but must be used within 6 hours [see Dosage and Administration (2.2)].

17 PATIENT COUNSELING INFORMATION

Thromboembolic Risk

Inform patients that reversing dabigatran therapy exposes them to the thromboembolic risk of their underlying disease. To reduce this risk, resumption of anticoagulant therapy should be considered as soon as the patient is sufficiently stable [see Warnings and Precautions (5.1)].

Recurrence of Bleeding

Inform patients to get immediate medical attention for any signs or symptoms of bleeding [see Warnings and Precautions (5.2)].

Hypersensitivity Reactions

Inform patients of signs and symptoms of allergic hypersensitivity reactions such as anaphylactoid reactions that may be experienced during or after injection of PRAXBIND [see Warnings and Precautions (5.3)].

Risk of Serious Adverse Reactions in Patients with Hereditary Fructose Intolerance due to Sorbitol Excipient

Inform patients with hereditary fructose intolerance (HFI) that PRAXBIND contains sorbitol. Parenteral administration of sorbitol in patients who have HFI has been associated with reports of hypoglycemia, hypophosphatemia, metabolic acidosis, increase in uric acid, acute liver failure with breakdown of excretory and synthetic function, and death and may occur during or after injection of PRAXBIND [see Warnings and Precautions (5.4)].

Boehringer Ingelheim Pharmaceuticals, Inc.
Ridgefield, CT 06877 USA
US License No. 2006

Product of Germany

Licensed from:
Boehringer Ingelheim International GmbH

Copyright © 2023 Boehringer Ingelheim International GmbH
ALL RIGHTS RESERVED

COL10514BJ272023
SPL10516B

PRINCIPAL DISPLAY PANEL - 50 mL Vial Label

NDC 0597-0197-05
Rx only

Praxbind®
(idarucizumab)
Injection

2.5 g/50 mL
(50 mg/mL)

For Intravenous Use Only
Discard Unused Portion.
Administer 2 vials for complete dose of 5 g
50 mL Single-Dose Vial

Boehringer
Ingelheim